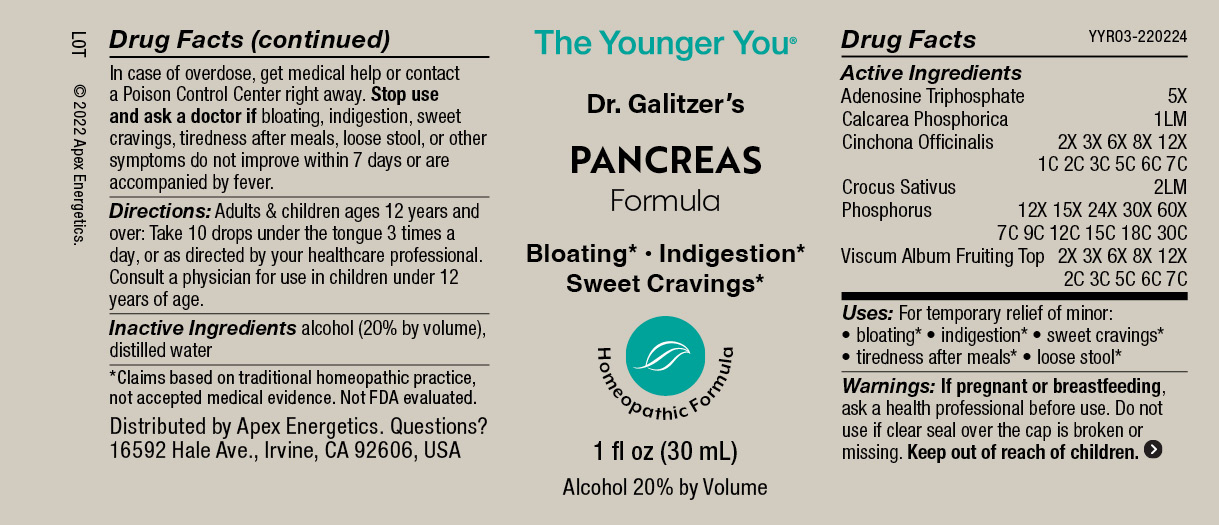 DRUG LABEL: PANCREAS Formula
NDC: 63479-2503 | Form: SOLUTION/ DROPS
Manufacturer: Apex Energetics Inc.
Category: homeopathic | Type: HUMAN OTC DRUG LABEL
Date: 20240108

ACTIVE INGREDIENTS: ADENOSINE TRIPHOSPHATE 5 [hp_X]/1 mL; SAFFRON 2 [hp_Q]/1 mL; TRIBASIC CALCIUM PHOSPHATE 1 [hp_Q]/1 mL; VISCUM ALBUM FRUITING TOP 7 [hp_C]/1 mL; CINCHONA OFFICINALIS BARK 7 [hp_C]/1 mL; PHOSPHORUS 30 [hp_C]/1 mL
INACTIVE INGREDIENTS: WATER; ALCOHOL

YYR03

Active Ingredients
Adenosine Triphosphate | 5X
Calcarea Phosphorica | 1LM
Cinchona Officinalis | 2X 3X 6X 8X 12X 1C 2C 3C 5C 6C 7C
Crocus Sativus | 2LM
Phosphorus | 12X 15X 24X 30X 60X 7C 9C 12C 15C 18C 30C
Viscum Album Fruiting Top | 2X 3X 6X 8X 12X 2C 3C 5C 6C 7C

Uses:

PURPOSE

For temporary relief of minor:

bloating*

indigestion*

sweet cravings*

tiredness after meals*

loose stool*

*Claims based on traditional homeopathic practice, not accepted medical evidence. Not FDA evaluated.

Warnings:

PREGNANCY OR BREAST FEEDING

If pregnant or breastfeeding, ask a health professional before use.

Do not use if clear seal over the cap is broken or missing.

Keep out of reach of children. In case of overdose, get medical help or contact a Poison Control Center right away.

Stop use and ask a doctor if bloating, indigestion, sweet cravings, tiredness after meals, loose stool, or other symptoms do not improve within 7 days or are accompanied by fever.

Directions:

Adults & children ages 12 years and over: Take 10 drops under the tongue 3 times a day, or as directed by your healthcare professional. Consult a physician for use in children under 12 years of age.

INACTIVE INGREDIENT

alcohol (20% by volume), distilled water

Distributed by Apex Energetics. Questions?

16592 Hale Ave., Irvine, CA 92606, USA

PACKAGE LABEL

The Younger You®

Dr. Galitzer’s

PANCREAS

Formula

Bloating* Indigestion*

Sweet Cravings*

Homeopathic Formula

1 fl oz (30 mL)

Alcohol 20% by Volume